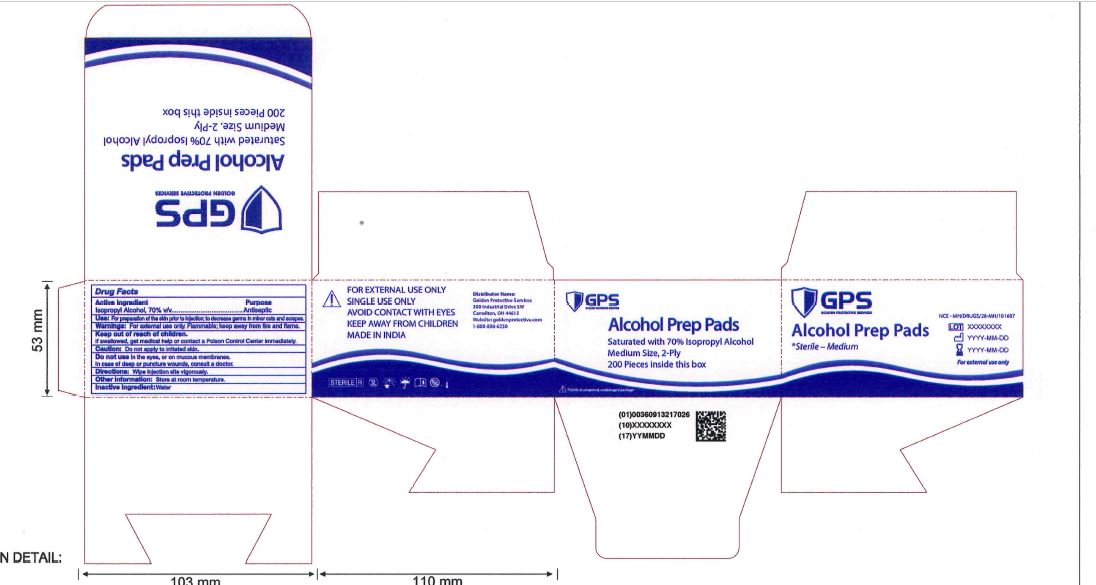 DRUG LABEL: Alcohol Prep Pads
NDC: 60913-217 | Form: SWAB
Manufacturer: Phoenix Healthcare Solutions, LLC
Category: otc | Type: HUMAN OTC DRUG LABEL
Date: 20251023

ACTIVE INGREDIENTS: ISOPROPYL ALCOHOL 70 mL/100 mL
INACTIVE INGREDIENTS: WATER

GPS APP Medium 200ct

ACTIVE INGREDIENT

Isopropyl Alcohol, 70% v/v

PURPOSE

Antiseptic

INDICATIONS AND USAGE

For Preparation of the skin prior to injection; to decrease germs in minor cuts and scrapes.

WARNINGS

For External Use only

Flammable, keep away from fire and flame.

DOSAGE AND ADMINISTRATION

Wipe Injection site vigorously.

STORAGE AND HANDLING

Store at Room Temperature.

INACTIVE INGREDIENT

Water

Keep out of reach of Children.

If swallowed, get medical help or contact a Poison Control Center Immediately.

Do not use in the eyes, or on mucous membranes.

Incase of deep or punture wounds, consult a Doctor.

OTHER SAFETY INFORMATION

Do not apply to irritated skin.